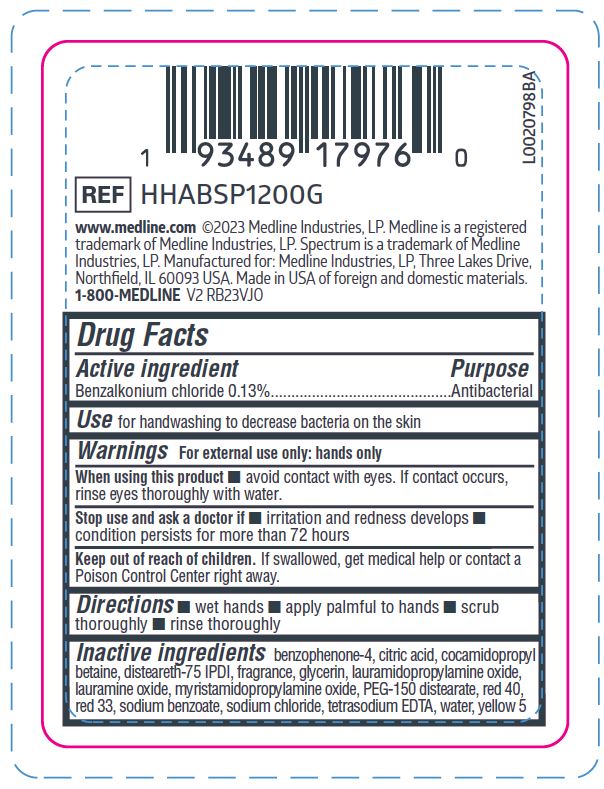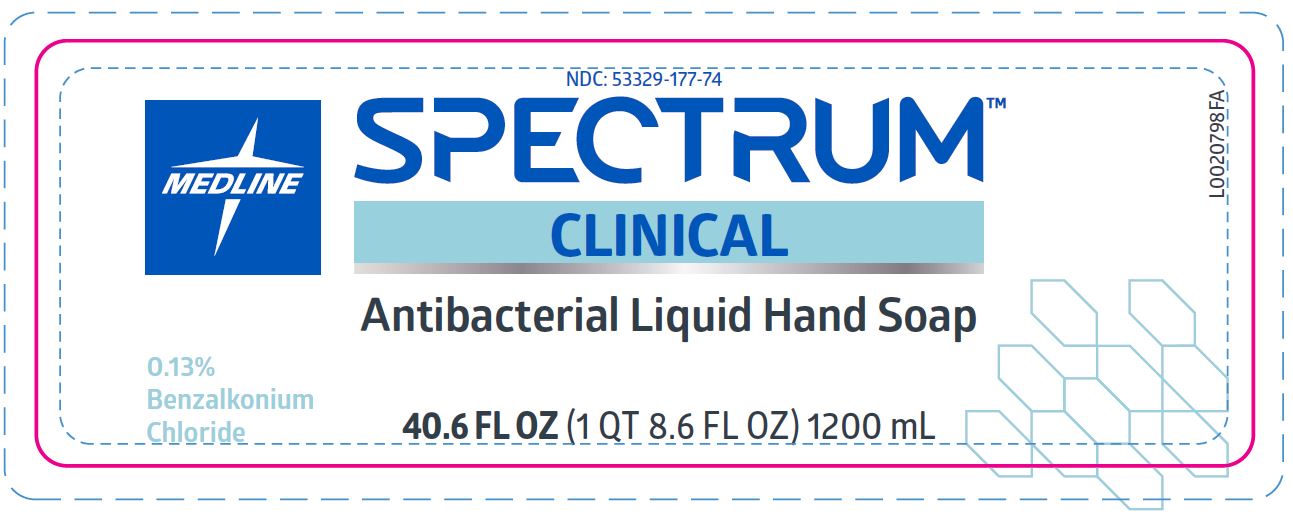 DRUG LABEL: Cleanse
NDC: 53329-177 | Form: SOLUTION
Manufacturer: Medline Industries, LP
Category: otc | Type: HUMAN OTC DRUG LABEL
Date: 20260211

ACTIVE INGREDIENTS: BENZALKONIUM CHLORIDE 0.13 g/100 mL
INACTIVE INGREDIENTS: SODIUM BENZOATE; COCAMIDOPROPYL BETAINE; LAURAMINE OXIDE; PEG-150 DISTEARATE; SULISOBENZONE; FD&C YELLOW NO. 5; FD&C RED NO. 40; D&C RED NO. 33; EDETATE SODIUM; GLYCERIN; DISTEARETH-75 ISOPHORONE DIISOCYANATE; SODIUM CHLORIDE; CITRIC ACID MONOHYDRATE; LAURAMIDOPROPYLAMINE OXIDE; WATER; MYRISTAMIDOPROPYLAMINE OXIDE

177 Antibacterial Hand Soap

Active ingredient

Benzalkonium chloride 0.13%

Purpose

Antibacterial

Use

for handwashing to decrease bacteria on the skin

Warnings

For external use only: hands only

When using this product

- avoid contact with the eyes. If contact occurs, rinse eyes thoroughly with water.

Stop use and ask a doctor if

- irritation and redness develops
- condition persists for more than 72 hours

Keep out of reach of children.

If swallowed, get medical help or contact a Poison Control Center right away.

Directions

- wet hands
- apply palmful to hands
- scrub thoroughly
- rinse thoroughly

Inactive ingredients

benzophenone-4, citric acid, cocamidopropyl betaine, disteareth-75 IPDI, fragrance, glycerin, lauramidopropylamine oxide, lauramine oxide, myristamidopropylamine oxide, PEG-150 distearate, red 40, red 33, sodium benzoate, sodium chloride, tetrasodium EDTA, water, yellow 5

Manufacturing Information

www.medline.com

©2023 Medline Industries, LP.

Medline is a registered trademark of Medline Industries, LP.

Spectrum is a trademark of Medline Industries, LP.

Manufactured for Medline Industries, LP

Three Lakes Drive, Northfield, IL 60093, USA

Made in USA of foreign and domestic materials

1-800-MEDLINE

REF: HHABSP1200G